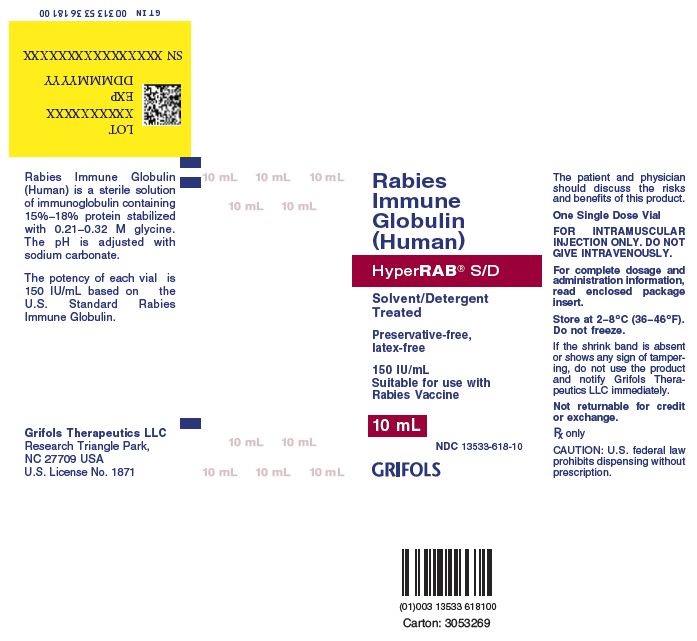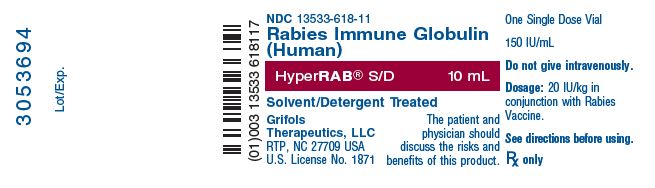 DRUG LABEL:  HYPERRAB 
NDC: 13533-618 | Form: INJECTION
Manufacturer: GRIFOLS USA, LLC
Category: other | Type: PLASMA DERIVATIVE
Date: 20221109

ACTIVE INGREDIENTS: Human Rabies Virus Immune Globulin 150 [iU]/1 mL
INACTIVE INGREDIENTS: Glycine; Water

Rabies Immune Globulin (Human)
HyperRAB® S/D
Solvent/Detergent Treated

DESCRIPTION

Rabies Immune Globulin (Human) — HyperRAB® S/D treated with solvent/detergent is a colorless to pale yellow or pink sterile solution of antirabies immune globulin for intramuscular administration; it is preservative-free and latex-free. HyperRAB S/D is prepared by cold ethanol fractionation from the plasma of donors hyperimmunized with rabies vaccine. The immune globulin is isolated from solubilized Cohn Fraction II. The Fraction II solution is adjusted to a final concentration of 0.3% tri-n-butyl phosphate (TNBP) and 0.2% sodium cholate. After the addition of solvent (TNBP) and detergent (sodium cholate), the solution is heated to 30°C and maintained at that temperature for not less than 6 hours. After the viral inactivation step, the reactants are removed by precipitation, filtration and finally ultrafiltration and diafiltration. HyperRAB S/D is formulated as a 15–18% protein solution at a pH of 6.4–7.2 in 0.21–0.32 M glycine. HyperRAB S/D is then incubated in the final container for 21–28 days at 20–27°C. The product is standardized against the U.S. Standard Rabies Immune Globulin to contain an average potency value of 150 IU/mL. The U.S. unit of potency is equivalent to the international unit (IU) for rabies antibody.

The removal and inactivation of spiked model enveloped and non-enveloped viruses during the manufacturing process for HyperRAB S/D has been validated in laboratory studies. Human Immunodeficiency Virus, Type 1 (HIV-1), was chosen as the relevant virus for blood products; Bovine Viral Diarrhea Virus (BVDV) was chosen to model Hepatitis C virus; Pseudorabies virus (PRV) was chosen to model Human Herpes viruses and other large enveloped DNA viruses; and Reo virus type 3 (Reo) was chosen to model non-enveloped viruses and for its resistance to physical and chemical inactivation. Significant removal of model enveloped and non-enveloped viruses is achieved at two steps in the Cohn fractionation process leading to the collection of Cohn Fraction II: the precipitation and removal of Fraction III in the processing of Fraction II + IIIW suspension to Effluent III and the filtration step in the processing of Effluent III to Filtrate III. Significant inactivation of enveloped viruses is achieved at the time of treatment of solubilized Cohn Fraction II with TNBP/sodium cholate.

Additionally, the manufacturing process was investigated for its capacity to decrease the infectivity of an experimental agent of transmissible spongiform encephalopathy (TSE), considered as a model for the vCJD and CJD agents. [27-30]

Studies of the HyperRAB S/D manufacturing process demonstrate that TSE clearance is achieved during the Pooled Plasma to Effluent III Fractionation Process (6.7 log10). These studies provide reasonable assurance that low levels of CJD/vCJD agent infectivity, if present in the starting material, would be removed.

CLINICAL PHARMACOLOGY

The usefulness of prophylactic rabies antibody in preventing rabies in humans when administered immediately after exposure was dramatically demonstrated in a group of persons bitten by a rabid wolf in Iran. [1,2] Similarly, beneficial results were later reported from the U.S.S.R. [3] Studies coordinated by WHO (World Health Organization) helped determine the optimal conditions under which antirabies serum of equine origin and rabies vaccine can be used in man. [4-7] These studies showed that serum can interfere to a variable extent with the active immunity induced by the vaccine, but could be minimized by booster doses of vaccine after the end of the usual dosage series.

Preparation of rabies immune globulin of human origin with adequate potency was reported by Cabasso et al. [8] In carefully controlled clinical studies, this globulin was used in conjunction with rabies vaccine of duck-embryo origin (DEV). [8,9] These studies determined that a human globulin dose of 20 IU/kg of rabies antibody, given simultaneously with the first DEV dose, resulted in amply detectable levels of passive rabies antibody 24 hours after injection in all recipients. The injections produced minimal, if any, interference with the subject’s endogenous antibody response to DEV.

More recently, human diploid cell rabies vaccines (HDCV) prepared from tissue culture fluids containing rabies virus have received substantial clinical evaluation in Europe and the United States. [10-16] In a study in adult volunteers, the administration of Rabies Immune Globulin (Human) did not interfere with antibody formation induced by HDCV when given in a dose of 20 IU per kilogram body weight simultaneously with the first dose of vaccine. [15]

In a clinical study in eight healthy human adults receiving a 20 IU/kg intramuscular dose of Rabies Immune Globulin (Human) treated with solvent/detergent, HyperRAB S/D, detectable passive rabies antibody titers were observed in the serum of all subjects by 24 hours post injection and persisted through the 21 day study period. These results are consistent with prior studies [17,18] with non-solvent/detergent treated product.

INDICATIONS AND USAGE

Rabies vaccine and HyperRAB S/D should be given to all persons suspected of exposure to rabies with one exception: persons who have been previously immunized with rabies vaccine and have a confirmed adequate rabies antibody titer should receive only vaccine. HyperRAB S/D should be administered as promptly as possible after exposure, but can be administered up to the eighth day after the first dose of vaccine is given.

Recommendations for use of passive and active immunization after exposure to an animal suspected of having rabies have been detailed by the U.S. Public Health Service Advisory Committee on Immunization Practices (ACIP). [19]

Every exposure to possible rabies infection must be individually evaluated. The following factors should be considered before specific antirabies treatment is initiated:

1. Species of Biting Animal

Carnivorous wild animals (especially skunks, foxes, coyotes, raccoons, and bobcats) and bats are the animals most commonly infected with rabies and have caused most of the indigenous cases of human rabies in the United States since 1960. [20] Unless the animal is tested and shown not to be rabid, postexposure prophylaxis should be initiated upon bite or nonbite exposure to these animals (see item 3 below). If treatment has been initiated and subsequent testing in a competent laboratory shows the exposing animal is not rabid, treatment can be discontinued.

In the United States, the likelihood that a domestic dog or cat is infected with rabies varies from region to region; hence, the need for postexposure prophylaxis also varies. However, in most of Asia and all of Africa and Latin America, the dog remains the major source of human exposure; exposures to dogs in such countries represent a special threat. Travelers to those countries should be aware that >50% of the rabies cases among humans in the United States result from exposure to dogs outside the United States.

Rodents (such as squirrels, hamsters, guinea pigs, gerbils, chipmunks, rats, and mice) and lagomorphs (including rabbits and hares) are rarely found to be infected with rabies and have not been known to cause human rabies in the United States. However, from 1971 through 1988, woodchucks accounted for 70% of the 179 cases of rabies among rodents reported to CDC. [21] In these cases, the state or local health department should be consulted before a decision is made to initiate postexposure antirabies prophylaxis.

2. Circumstances of Biting Incident

An unprovoked attack is more likely to mean that the animal is rabid. (Bites during attempts to feed or handle an apparently healthy animal may generally be regarded as provoked.)

3. Type of Exposure

Rabies is transmitted only when the virus is introduced into open cuts or wounds in skin or mucous membranes. If there has been no exposure (as described in this section), postexposure treatment is not necessary. Thus, the likelihood that rabies infection will result from exposure to a rabid animal varies with the nature and extent of the exposure. Two categories of exposure should be considered:

Bite: any penetration of the skin by teeth. Bites to the face and hands carry the highest risk, but the site of the bite should not influence the decision to begin treatment. [22]

Bat-associated strains of rabies can be transmitted to humans either directly through a bat's bite or indirectly through the bite of an animal previously infected by a bat. Because some bat bites may be less severe, and can go completely undetected, unlike bites inflicted by larger animals, especially mammalian carnivores, rabies postexposure treatment should be considered for any physical contact with bats when bite or mucous membrane contact cannot be excluded. [23]

Nonbite: scratches, abrasions, open wounds or mucous membranes contaminated with saliva or any potentially infectious material, such as brain tissue, from a rabid animal constitute nonbite exposures. If the material containing the virus is dry, the virus can be considered noninfectious. Casual contact, such as petting a rabid animal and contact with the blood, urine, or feces (e.g., guano) of a rabid animal, does not constitute an exposure and is not an indication for prophylaxis. Instances of airborne rabies have been reported rarely. Adherence to respiratory precautions will minimize the risk of airborne exposure. [24]

The only documented cases of rabies from human-to-human transmission have occurred in patients who received corneas transplanted from persons who died of rabies undiagnosed at the time of death. Stringent guidelines for acceptance of donor corneas have reduced this risk.

Bite and nonbite exposures from humans with rabies theoretically could transmit rabies, although no cases of rabies acquired this way have been documented.

4. Vaccination Status of Biting Animal

A properly immunized animal has only a minimal chance of developing rabies and transmitting the virus.

5. Presence of Rabies in Region

If adequate laboratory and field records indicate that there is no rabies infection in a domestic species within a given region, local health officials are justified in considering this in making recommendations on antirabies treatment following a bite by that particular species. Such officials should be consulted for current interpretations.

Rabies Postexposure Prophylaxis

The following recommendations are only a guide. In applying them, take into account the animal species involved, the circumstances of the bite or other exposure, the vaccination status of the animal, and presence of rabies in the region. Local or state public health officials should be consulted if questions arise about the need for rabies prophylaxis.

Local Treatment of Wounds: Immediate and thorough washing of all bite wounds and scratches with soap and water is perhaps the most effective measure for preventing rabies. In experimental animals, simple local wound cleansing has been shown to reduce markedly the likelihood of rabies.

Tetanus prophylaxis and measures to control bacterial infection should be given as indicated.
Active Immunization: Active immunization should be initiated as soon as possible after exposure (within 24 hours). Many dosage schedules have been evaluated for the currently available rabies vaccines and their respective manufacturers’ literature should be consulted.
Passive Immunization: A combination of active and passive immunization (vaccine and immune globulin) is considered the acceptable postexposure prophylaxis except for those persons who have been previously immunized with rabies vaccine and who have documented adequate rabies antibody titer. These individuals should receive vaccine only. For passive immunization, Rabies Immune Globulin (Human) is preferred over antirabies serum, equine. [16,19] It is recommended both for treatment of all bites by animals suspected of having rabies and for nonbite exposure inflicted by animals suspected of being rabid. Rabies Immune Globulin (Human) should be used in conjunction with rabies vaccine and can be administered through the seventh day after the first dose of vaccine is given. Beyond the seventh day, Rabies Immune Globulin (Human) is not indicated since an antibody response to cell culture vaccine is presumed to have occurred.

Rabies Postexposure Prophylaxis Guide [19]
Animal species | Condition of animal at time of exposure/attack | Treatment of exposed person [ALL POSTEXPOSURE PROPHYLAXIS SHOULD BEGIN WITH IMMEDIATE THOROUGH CLEANSING OF THE WOUND (IF ONE CAN BE DETECTED) WITH SOAP AND WATER. If antirabies treatment is indicated, both Rabies Immune Globulin (Human) [RIGH] and human diploid cell rabies vaccine (HDCV) should be given as soon as possible, REGARDLESS of the interval from exposure.]
Dog and cat | Healthy and available for 10 days of observation | None, unless animal develops rabies [During the usual holding period of 10 days, begin postexposure prophylaxis at first sign of rabies in a dog or cat that has bitten someone. If the animal exhibits clinical signs of rabies, it should be euthanized immediately and tested.]
Dog and cat | Rabid or suspected rabid | RIGH [If RIGH is not available, use antirabies serum, equine (ARS). Do not use more than the recommended dosage.] and HDCV
Dog and cat | Unknown (escaped) | Consult public health officials
Skunk, bat, fox, coyote, raccoon, bobcat, and other carnivores; woodchuck | Regard as rabid unless animal proven negative by laboratory tests [The animal should be euthanized and tested as soon as possible. Holding for observation is not recommended. Discontinue vaccine if immunofluorescence test results of the animal are negative.] | RIGH and HDCV
Livestock, rodents, and lagomorphs (rabbits and hares) | Consider individually. Local and state public health officials should be consulted on questions about the need for rabies prophylaxis. In most geographical areas bites of squirrels, hamsters, guinea pigs, gerbils, chipmunks, rats, mice, other rodents, rabbits, and hares almost never require antirabies postexposure prophylaxis.

CONTRAINDICATIONS

None known.

WARNINGS

Rabies Immune Globulin (Human) — HyperRAB® S/D is made from human plasma. Products made from human plasma may contain infectious agents, such as viruses, and, theoretically, the Creutzfeldt-Jakob Disease (CJD) agent that can cause disease. The risk that such products will transmit an infectious agent has been reduced by screening plasma donors for prior exposure to certain viruses, by testing for the presence of certain current virus infections, and by inactivating and/or removing certain viruses. Despite these measures, such products can still potentially transmit disease. There is also the possibility that unknown infectious agents may be present in such products. Individuals who receive infusions of blood or plasma products may develop signs and/or symptoms of some viral infections, particularly hepatitis C. ALL infections thought by a physician possibly to have been transmitted by this product should be reported by the physician or other healthcare provider to Grifols Therapeutics LLC [1-800-520-2807].

The physician should discuss the risks and benefits of this product with the patient, before prescribing or administering it to the patient.

HyperRAB S/D should be given with caution to patients with a history of prior systemic allergic reactions following the administration of human immunoglobulin preparations.

The attending physician who wishes to administer HyperRAB S/D to persons with isolated immunoglobulin A (IgA) deficiency must weigh the benefits of immunization against the potential risks of hypersensitivity reactions. Such persons have increased potential for developing antibodies to IgA and could have anaphylactic reactions to subsequent administration of blood products that contain IgA. [25]

As with all preparations administered by the intramuscular route, bleeding complications may be encountered in patients with thrombocytopenia or other bleeding disorders.

PRECAUTIONS

General

HyperRAB S/D should not be administered intravenously because of the potential for serious reactions. Although systemic reactions to immunoglobulin preparations are rare, epinephrine should be available for treatment of acute anaphylactoid symptoms.

Drug Interactions

Repeated doses of HyperRAB S/D should not be administered once vaccine treatment has been initiated as this could prevent the full expression of active immunity expected from the rabies vaccine.

Other antibodies in the HyperRAB S/D preparation may interfere with the response to live vaccines such as measles, mumps, polio or rubella. Therefore, immunization with live vaccines should not be given within 3 months after HyperRAB S/D administration.

Pregnancy

Animal reproduction studies have not been conducted with HyperRAB S/D. It is also not known whether HyperRAB S/D can cause fetal harm when administered to a pregnant woman or can affect reproduction capacity. HyperRAB S/D should be given to a pregnant woman only if clearly needed.

Pediatric Use

Safety and effectiveness in the pediatric population have not been established.

ADVERSE REACTIONS

Soreness at the site of injection and mild temperature elevations may be observed at times. Sensitization to repeated injections has occurred occasionally in immunoglobulin-deficient patients. Angioneurotic edema, skin rash, nephrotic syndrome, and anaphylactic shock have rarely been reported after intramuscular injection, so that a causal relationship between immunoglobulin and these reactions is not clear.

DOSAGE AND ADMINISTRATION

The recommended dose for HyperRAB S/D is 20 IU/kg (0.133 mL/kg) of body weight given preferably at the time of the first vaccine dose.[8,9] It may also be given through the seventh day after the first dose of vaccine is given. If anatomically feasible, up to the full dose of HyperRAB S/D should be thoroughly infiltrated in the area around the wound and the rest should be administered intramuscularly in the deltoid muscle of the upper arm or lateral thigh muscle. The gluteal region should not be used as an injection site because of the risk of injury to the sciatic nerve. [26] HyperRAB S/D should never be administered in the same syringe or needle or in the same anatomical site as vaccine.

Parenteral drug products should be inspected visually for particulate matter and discoloration prior to administration, whenever solution and container permit.

Rabies postexposure prophylaxis schedule—United States, 1999 [19]
Vaccination status | Treatment | Regimen [These regimens are applicable for all age groups, including children.]
Not previously vaccinated | Wound cleansing | All postexposure treatment should begin with immediate thorough cleansing of all wounds with soap and water. If available, a virucidal agent such as a povidone-iodine solution should be used to irrigate the wounds.
Not previously vaccinated | RIG | Administer 20 IU/kg body weight. If anatomically feasible, the full dose should be infiltrated around the wound(s) and any remaining volume should be administered IM at an anatomical site distant from vaccine administration. Also, RIG should not be administered in the same syringe as vaccine. Because RIG might partially suppress active production of antibody, no more than the recommended dose should be given.
Not previously vaccinated | Vaccine | HDCV, RVA, or PCEC 1.0 mL, IM (deltoid area [The deltoid area is the only acceptable site of vaccination for adults and older children. For younger children, the outer aspect of the thigh may be used. Vaccine should never be administered in the gluteal area.]), one each on days 0 [Day 0 is the day the first dose of vaccine is administered.] , 3, 7, 14, and 28.
Previously vaccinated [Any person with a history of preexposure vaccination with HDCV, RVA, or PCEC; prior postexposure prophylaxis with HDCV, RVA, or PCEC; or previous vaccination with any other type of rabies vaccine and a documented history of antibody response to the prior vaccination.] | Wound cleansing | All postexposure treatment should begin with immediate thorough cleansing of all wounds with soap and water. If available, a virucidal agent such as a povidone-iodine solution should be used to irrigate the wounds.
Previously vaccinated [Any person with a history of preexposure vaccination with HDCV, RVA, or PCEC; prior postexposure prophylaxis with HDCV, RVA, or PCEC; or previous vaccination with any other type of rabies vaccine and a documented history of antibody response to the prior vaccination.] | RIG | RIG should not be administered.
 | Vaccine | HDCV, RVA, or PCEC 1.0 mL, IM (deltoid area), one each on days 0 and 3.
HDCV=human diploid cell vaccine; PCEC=purified chick embryo cell vaccine; RIG=rabies immune globulin; RVA=rabies vaccine adsorbed; IM, intramuscular

HOW SUPPLIED

HyperRAB S/D is packaged in 2 mL and 10 mL single dose vials with an average potency value of 150 international units per mL (IU/mL). The 2 mL vial contains a total of 300 IU which is sufficient for a child weighing 15 kg. The 10 mL vial contains a total of 1500 IU which is sufficient for an adult weighing 75 kg. HyperRAB S/D is preservative-free and latex-free.

NDC Number | Size
13533-618-02 | 2 mL vial
13533-618-10 | 10 mL vial

STORAGE

HyperRAB S/D should be stored under refrigeration (2–8°C, 36–46°F). Solution that has been frozen should not be used.

CAUTION

Rx only

U.S. federal law prohibits dispensing without prescription.

LIMITED WARRANTY

A number of factors could reduce the efficacy of this product or even result in an ill effect following its use. These include improper storage and handling of the product after it leaves our hands, diagnosis, dosage, method of administration, and biological differences in individual patients. Because of these factors, it is important that this product be stored properly and that the directions be followed carefully during use.

No warranty, express or implied, including any warranty of merchantability or fitness is made. Representatives of the Company are not authorized to vary the terms or the contents of the printed labeling, including the package insert for this product, except by printed notice from the Company’s headquarters. The prescriber and user of this product must accept the terms hereof.

REFERENCES

1. Baltazard M, Bahmanyar M, Ghodssi M, et al: Essai pratique du sérum antirabique chez les mordus par loups enragés. Bull WHO 13:747-72, 1955.
2. Habel K, Koprowski H: Laboratory data supporting the clinical trial of antirabies serum in persons bitten by a rabid wolf. Bull WHO 13:773-9, 1955.
3. Selimov M, Boltucij L, Semenova E, et al: [The use of antirabies gamma globulin in subjects severely bitten by rabid wolves or other animals.] J Hyg Epidemiol Microbiol Immunol (Praha) 3. 168-80, 1959.
4. Atanasiu P, Bahmanyar M, Baltazard M, et al: Rabies neutralizing antibody response to different schedules of serum and vaccine inoculations in non-exposed persons. Bull WHO 14:593-611, 1956.
5. Atanasiu P, Bahmanyar M, Baltazard M, et al: Rabies neutralizing antibody response to different schedules of serum and vaccine inoculations in non-exposed persons: Part II. Bull WHO 17:911-32, 1957.
6. Atanasiu P, Cannon DA, Dean DJ, et al: Rabies neutralizing antibody response to different schedules of serum and vaccine innoculations in non-exposed persons: Part 3. Bull WHO 25:103-14, 1961.
7. Atanasiu P, Dean DJ, Habel K, et al: Rabies neutralizing antibody response to different schedules of serum and vaccine inoculations in non-exposed persons: Part 4. Bull WHO 36:361-5, 1967.
8. Cabasso VJ, Loofbourow JC, Roby RE, et al: Rabies immune globulin of human origin: preparation and dosage determination in non-exposed volunteer subjects. Bull WHO 45:303-15, 1971.
9. Loofbourow JC, Cabasso VJ, Roby RE, et al: Rabies immune globulin (human): clinical trials and dose determination. JAMA 217(13): 1825-31, 1971.
10. Plotkin SA: New rabies vaccine halts disease — without severe reactions. Mod Med 45(20):45-8, 1977.
11. Plotkin SA, Wiktor TJ, Koprowski H, et al: Immunization schedules for the new human diploid cell vaccine against rabies. Am J Epidemiol 103(1):75-80, 1976.
12. Hafkin B, Hattwick MA, Smith JS, et al: A comparison of a WI-38 vaccine and duck embryo vaccine for preexposure rabies prophylaxis. Am J Epidemiol 107(5):439-43, 1978.
13. Kuwert EK, Marcus I, Höher PG: Neutralizing and complement-fixing antibody responses in pre- and post-exposure vaccinees to a rabies vaccine produced in human diploid cells. J Biol Stand 4(4):249-62, 1976.
14. Grandien M: Evaluation of tests for rabies antibody and analysis of serum responses after administration of three different types of rabies vaccines. J Clin Microbiol 5(3):263-7, 1977.
15. Kuwert EK, Marcus I, Werner J, et al: Postexpositionelle Schutzimpfung des Menschen gegen Tollwut mit einer neu-entwickelten Gewebekulturvakzine (HDCS-Impfstoff). Zentralbl Bakteriol [A] 239(4):437-58, 1977.
16. Bahmanyar M, Fayaz A, Nour-Salehi S, et al: Successful protection of humans exposed to rabies infection: postexposure treatment with the new human diploid cell rabies vaccine and antirabies serum. JAMA 236(24):2751-4, 1976.
17. American Hospital Formulary Service. Drug Information. Section 80:04. Rabies immune globulin. Bethesda, American Society for Health-Systems Pharmacy, 1997, p. 2545-7.
18. Rubin Rh, Sikes RK, Gregg MB: Human rabies immune globulin. Clinical trials and effects on serum anti-globulins. JAMA 224:871-4, 1973.
19. Recommendations of the Advisory Committee on Immunization Practices (ACIP): Rabies prevention—United States, 1999. MMWR 48 (RR-1):1-21, 1999.
20. Reid-Sanden FL, Dobbins JG, Smith JS, et al: Rabies surveillance in the United States during 1989. J Am Vet Med Assoc 197(12):1571-83, 1990.
21. Fishbein DB, Belotto AJ, Pacer RE, et al: Rabies in rodents and lagomorphs in the United States, 1971-1984: increased cases in the woodchuck (Marmota monax) in mid-Atlantic states. J Wildl Dis 22(2):151-5, 1986.
22. Hattwick MAW: Human rabies. Public Health Rev 3(3):229-74, 1974.
23. Epidemiologic Notes and Reports: Human Rabies—California, 1994. MMWR 43(25):455-457, 1994.
24. Garner JS, Simmons BP: Guideline for isolation precautions in hospitals. Infect Control 4(4 Suppl):245-325, 1983.
25. Fudenberg HH: Sensitization to immunoglobulins and hazards of gamma globulin therapy. In: Merler E (ed.): Immunoglobulins: biologic aspects and clinical uses. Washington, DC, Nat Acad Sci, 1970, pp 211-20.
26. Recommendations of the Advisory Committee on Immunization Practices (ACIP) and the American Academy of Family Physicians (AAFP): General recommendations on immunization. MMWR 2002: 51(RR02), 1-36.
27. Stenland CJ, Lee DC, Brown P, et al. Partitioning of human and sheep forms of the pathogenic prion protein during the purification of therapeutic proteins from human plasma. Transfusion 2002. 42(11):1497-500.
28. Lee DC, Stenland CJ, Miller JL, et al. A direct relationship between the partitioning of the pathogenic prion protein and transmissible spongiform encephalopathy infectivity during the purification of plasma proteins. Transfusion 2001. 41(4):449-55.
29. Lee DC, Stenland CJ, Hartwell RC, et al. Monitoring plasma processing steps with a sensitive Western blot assay for the detection of the prion protein. J Virol Methods 2000. 84(1):77-89.
30. Cai K, Miller JL, Stenland CJ, et al. Solvent-dependent precipitation of prion protein. Biochim Biophys Acta 2002. 1597(1):28-35.

(Rev. 6/2018)
Grifols Therapeutics LLC
Research Triangle Park, NC 27709 USA
U.S. License No. 1871
3052620

PACKAGE LABEL

Rabies Immune Globulin (Human)
HyperRAB®S/D
Solvent/Detergent Treated
Preservative-free, latex-free
150 IU/mL Suitable for use with Rabies Vaccine
10 mL
NDC 13533-618-10
GRIFOLS
The patient and physician should discuss the risks and benefits of this product.
One Single Dose Vial
FOR INTRAMUSCULAR INJECTION ONLY. DO NOT GIVE INTRAVENOUSLY.
For complete dosage and administration information, read enclosed package insert.
Store at 2–8ºC (36–46ºF).
Do not freeze.
If the shrink band is absent or shows any sign of tampering, do not use the product and notify Grifols Therapeutics LLC immediately.
Not returnable for credit or exchange.
Rx only
CAUTION: U.S. federal law prohibits dispensing without prescription.
Rabies Immune Globulin (Human) is a sterile solution of immunoglobulin containing 15%–18% protein stabilized with 0.21–0.32 M glycine. The pH is adjusted with sodium carbonate.
The potency of each vial is 150 IU/mL based on the U.S. Standard Rabies Immune Globulin.
Grifols Therapeutics LLC
Research Triangle Park, NC 27709 USA
U.S. License No. 1871
Carton: 3053269
GTIN 00313533618100
LOT
XXXXXXXXXX
EXP
DDMMMYYYY
SN XXXXXXXXXXXXXXXX

NDC 13533-618-11
Rabies Immune Globulin (Human)
HyperRAB® S/D
10 mL
Solvent/Detergent Treated
Grifols Therapeutics, LLC
RTP, NC 27709 USA
U.S. License No. 1871
The patient and physician should discuss the risks and benefits of this product.
One Single Dose Vial
150 IU/mL
Do not give intravenously.
Dosage: 20 IU/kg in conjunction with Rabies Vaccine.
See directions before using.
Rx only
3053694
Lot/Exp.